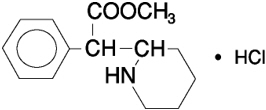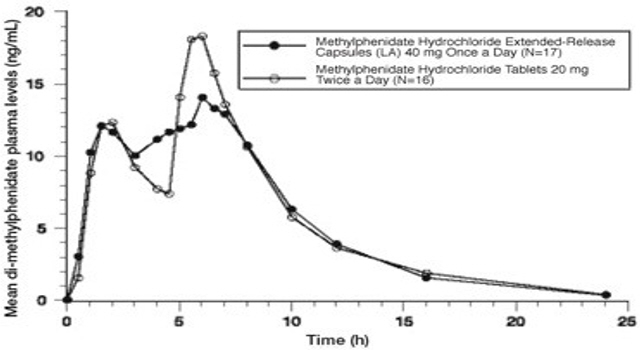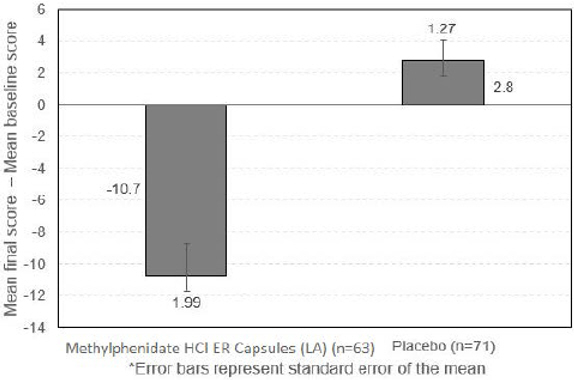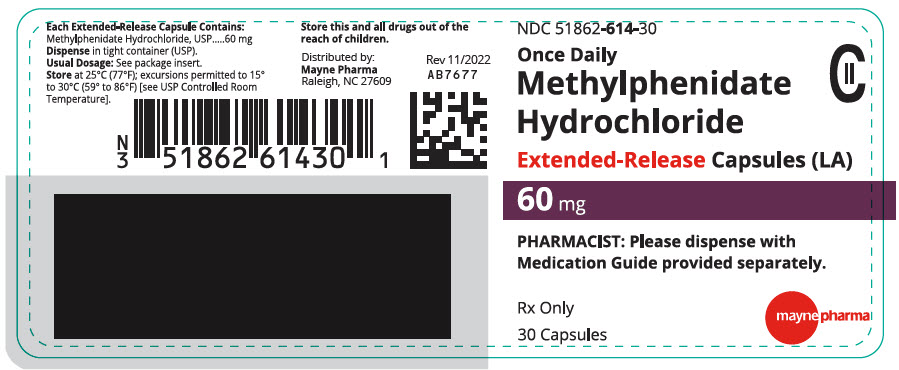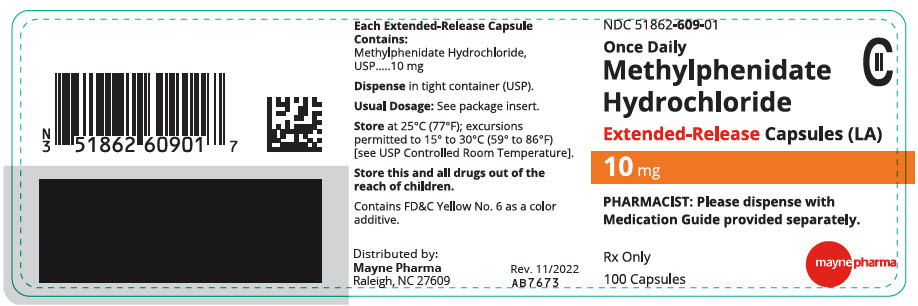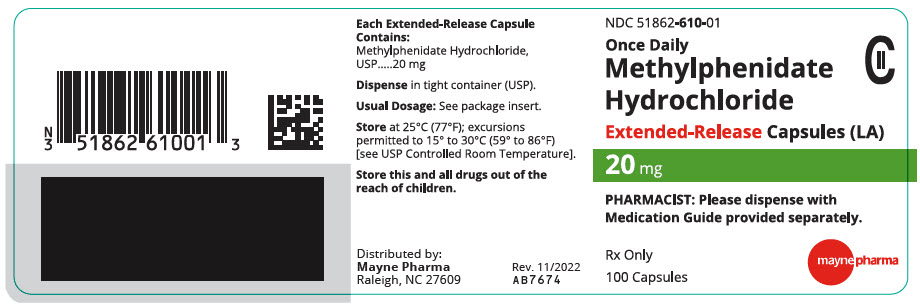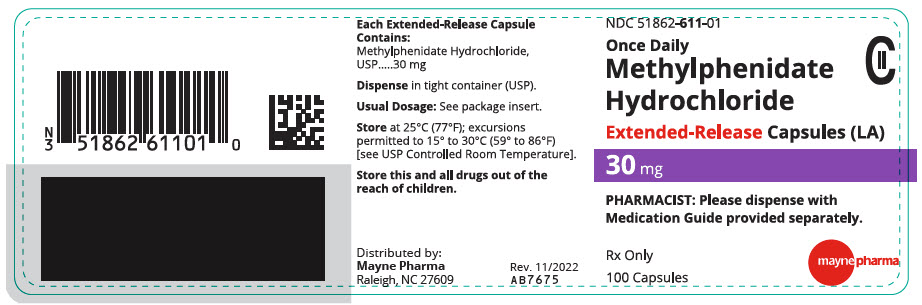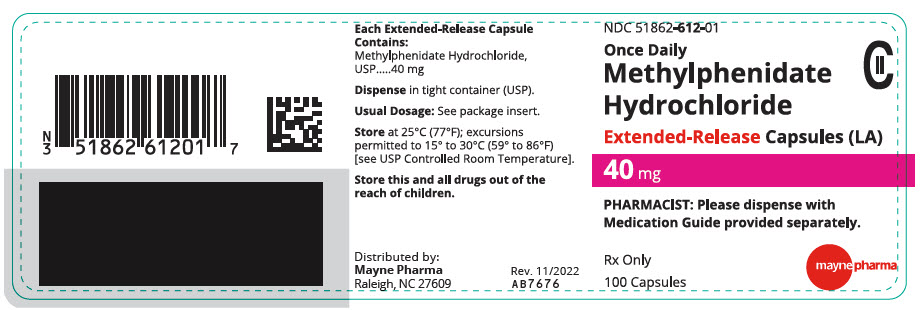 DRUG LABEL: Methylphenidate Hydrochloride (LA)
NDC: 51862-614 | Form: CAPSULE, EXTENDED RELEASE
Manufacturer: Mayne Pharma
Category: prescription | Type: HUMAN PRESCRIPTION DRUG LABEL
Date: 20251106
DEA Schedule: CII

ACTIVE INGREDIENTS: METHYLPHENIDATE HYDROCHLORIDE 60 mg/1 1
INACTIVE INGREDIENTS: SUCROSE; STARCH, CORN; HYPROMELLOSE, UNSPECIFIED; CELLULOSE ACETATE; HYPROMELLOSE ACETATE SUCCINATE 12070923 (3 MM2/S); ACETYLTRIBUTYL CITRATE; ACETONE; TALC; WATER; TITANIUM DIOXIDE; GELATIN, UNSPECIFIED; FERROSOFERRIC OXIDE; SHELLAC; POTASSIUM HYDROXIDE; FERRIC OXIDE YELLOW; AMMONIA; PROPYLENE GLYCOL

HIGHLIGHTS OF PRESCRIBING INFORMATION

These highlights do not include all the information needed to use METHYLPHENIDATE HYDROCHLORIDE EXTENDED-RELEASE CAPSULES (LA) safely and effectively. See full prescribing information for METHYLPHENIDATE HYDROCHLORIDE EXTENDED-RELEASE CAPSULES (LA).
METHYLPHENIDATE HYDROCHLORIDE extended-release capsules (LA) for oral use, CII
Initial U.S. Approval: 1955

WARNING: ABUSE AND DEPENDENCE

See full prescribing information for complete boxed warning.

- CNS stimulants, including methylphenidate hydrochloride extended-release capsules (LA), other methylphenidate- containing products, and amphetamines, have a high potential for abuse and dependence (5.1, 9.2, 9.3).
- Assess the risk of abuse prior to prescribing, and monitor for signs of abuse and dependence while on therapy (5.1, 9.2)

1 INDICATIONS AND USAGE

Methylphenidate hydrochloride extended-release capsules (LA) is a central nervous system (CNS) stimulant indicated for the treatment of Attention Deficit Hyperactivity Disorder (ADHD) in pediatric patients 6 to 12 years of age (1).

2 DOSAGE AND ADMINISTRATION

- Administer orally once daily in the morning (2.2).
- Capsules may be swallowed whole, or opened and the entire contents sprinkled on applesauce (2.2).
- Should not be crushed, chewed, or divided (2.2).
- Patients new to methylphenidate: Start at 20 mg daily, titrating the dose weekly in 10-mg increments. Doses above 60 mg daily are not recommended (2.3).
- For patients currently using methylphenidate hydrochloride tablets or methylphenidate hydrochloride extended-release tablets: Dosage is based on current dose regimen (2.4).
- If switching from other methylphenidate products, discontinue treatment and titrate with methylphenidate hydrochloride extended-release capsules (LA) (2.4).

3 DOSAGE FORMS AND STRENGTHS

Extended-release capsules: 10, 20, 30, 40, 60 mg (3).

4 CONTRAINDICATIONS

- Known hypersensitivity to methylphenidate or product components (4).
- Concurrent treatment with a monoamine oxidase inhibitor (MAOI), or use of an MAOI within the preceding 14 days (4).

5 WARNINGS AND PRECAUTIONS

- Serious Cardiovascular Events: Sudden death has been reported in association with CNS-stimulant treatment at usual doses in pediatric patients with structural cardiac abnormalities or other serious heart problems. In adults, sudden death, stroke, and myocardial infarction have been reported. Avoid use in patients with known structural cardiac abnormalities, cardiomyopathy, serious heart rhythm arrhythmias, or coronary artery disease (5.2).
- Blood Pressure and Heart Rate Increases: Monitor blood pressure and pulse. Consider the benefits and risk in patients for whom an increase in blood pressure or heart rate would be problematic (5.3).
- Psychiatric Adverse Reactions: Use of stimulants may cause psychotic or manic symptoms in patients with no prior history or exacerbation of symptoms in patients with preexisting psychiatric illness. Evaluate for preexisting psychotic or bipolar disorder prior to methylphenidate hydrochloride extended-release capsules (LA) use (5.4).
- Priapism: Cases of painful and prolonged penile erections and priapism have been reported with methylphenidate products. Immediate medical attention should be sought if signs or symptoms of prolonged penile erections or priapism are observed (5.5).
- Peripheral Vasculopathy, including Raynaud's Phenomenon: Stimulants used to treat ADHD are associated with peripheral vasculopathy, including Raynaud's phenomenon. Careful observation for digital changes is necessary during treatment with ADHD stimulants (5.6).
- Long-Term Suppression of Growth: Monitor height and weight at appropriate intervals in pediatric patients (5.7).

6 ADVERSE REACTIONS

Most common adverse reactions (greater than 5% during incidence) were headache, insomnia, upper abdominal pain, decreased appetite and anorexia (6).

To report SUSPECTED ADVERSE REACTIONS, contact Mayne Pharma at 1-844-825-8500 or FDA at 1-800-FDA-1088 or www.fda.gov/medwatch.

7 DRUG INTERACTIONS

- Antihypertensive drugs: Monitor blood pressure and heart. Adjust dosage of antihypertensive drug as needed (7.1).
- Halogenated Anesthetics:Avoid use of methylphenidate hydrochloride extended-release capsules (LA) on the day of surgery if halogenated anesthetics will be used (7.1).

FULL PRESCRIBING INFORMATION

WARNING: ABUSE AND DEPENDENCE

CNS stimulants, including methylphenidate hydrochloride extended-release capsules (LA), other methylphenidate-containing products, and amphetamines, have a high potential for abuse and dependence. Assess the risk of abuse prior to prescribing, and monitor for signs of abuse and dependence while on therapy [see Warning and Precautions (5.1), Drug Abuse and Dependence (9.2, 9.3)] .

1 INDICATIONS AND USAGE

Methylphenidate hydrochloride extended-release capsules (LA) is indicated for the treatment of Attention Deficit Hyperactivity Disorder (ADHD), in pediatric patients 6 to 12 years of age [see Clinical Studies (14)] .

2 DOSAGE AND ADMINISTRATION

2.1 Pretreatment Screening

Prior to initiating treatment with central nervous system (CNS) stimulants, including methylphenidate hydrochloride extended-release capsules (LA), assess for the presence of cardiac disease (i.e., perform a careful history, including family history of sudden death or ventricular arrhythmia, and physical examination) [see Warnings and Precautions (5.2)] .

Assess the risk of abuse prior to prescribing, and monitor for signs of abuse and dependence while on therapy. Maintain careful prescription records, educate patients about abuse, monitor for signs of abuse and overdose, and periodically reevaluate the need for methylphenidate hydrochloride extended-release capsules (LA) use [see Boxed Warning, Warnings and Precautions (5.1), Drug Abuse and Dependence (9.2, 9.3)].

2.2 General Dosing Information

The recommended starting dose for methylphenidate hydrochloride extended-release capsules (LA) is 20 mg once daily. Increase dosage gradually, in increments of 10 mg weekly. Daily dosage above 60 mg is not recommended. When a lower initial dose is appropriate, patients may begin treatment with 10 mg.

Administer methylphenidate hydrochloride extended-release capsules (LA) orally once daily in the morning. Methylphenidate hydrochloride extended-release capsules (LA) may be swallowed as whole capsules or may be administered by sprinkling the capsule contents on a small amount of applesauce (see specific instructions below). Methylphenidate hydrochloride extended-release capsules (LA) and/or their contents should not be crushed, chewed, or divided.

The capsules may be carefully opened and the beads sprinkled over a spoonful of applesauce. The applesauce should not be warm because it could affect the modified release properties of this formulation. The mixture of drug and applesauce should be consumed immediately in its entirety. The drug and applesauce mixture should not be stored for future use.

Pharmacological treatment of ADHD may be needed for extended periods. Periodically reevaluate the long-term use of methylphenidate hydrochloride tablets and methylphenidate hydrochloride extended-release tablets, and adjust dosage as needed.

2.3 Patients Currently Using Methylphenidate Hydrochloride Tablets or Methylphenidate Hydrochloride Extended-Release Tablets

The recommended dose of methylphenidate hydrochloride extended-release capsules (LA) for patients currently taking methylphenidate hydrochloride tablets twice daily or methylphenidate hydrochloride extended-release tablets (SR) is provided below.

TABLE 1: Recommended Dose Conversion From Methylphenidate Hydrochloride Tablets or Methylphenidate Hydrochloride Extended-Release Tablets
Previous Methylphenidate Hydrochloride Tablets or Methylphenidate Hydrochloride Extended-Release Tablets Dose | Recommended Methylphenidate Hydrochloride Extended-Release Capsules (LA) Dose
5 mg methylphenidate hydrochloride tablets twice daily | 10 mg once daily
10 mg methylphenidate hydrochloride tablets twice daily or 20 mg methylphenidate hydrochloride extended-release tablets | 20 mg once daily
15 mg methylphenidate hydrochloride tablets twice daily | 30 mg once daily
20 mg methylphenidate hydrochloride tablets twice daily or 40 mg of methylphenidate hydrochloride extended-release tablets | 40 mg once daily
30 mg methylphenidate hydrochloride tablets twice daily or 60 mg of methylphenidate hydrochloride extended-release tablets | 60 mg once daily

2.4 Switching From Other Methylphenidate Products

If switching from other methylphenidate products, discontinue that treatment, and titrate with methylphenidate hydrochloride extended-release capsules (LA) using the titration schedule.

Do not substitute for other methylphenidate products on a milligram-per-milligram basis, because different methylphenidate base compositions and differing pharmacokinetic profiles [see Description (11), Clinical Pharmacology (12.3)] .

Clinical judgment should be used when selecting the starting dose. Daily dosage above 60 mg is not recommended.

2.5 Dose Reduction and Discontinuation

If paradoxical worsening of symptoms or other adverse reactions occur, reduce the dosage, or, if necessary, discontinue methylphenidate hydrochloride extended-release capsules (LA). If improvement is not observed after appropriate dosage adjustment over a one-month period, the drug should be discontinued.

3 DOSAGE FORMS AND STRENGTHS

- 10 mg extended-release capsules white/light green (imprinted mayne 609 on both the body and cap)
- 20 mg extended-release capsules white/white (imprinted mayne 610 on both the body and cap)
- 30 mg extended-release capsules white/light blue, (imprinted mayne 611 on both body and cap)
- 40 mg extended-release capsules white/dark blue, (imprinted mayne 612 on both body and cap)
- 60 mg extended-release capsules light yellow/dark yellow (imprinted mayne 614 on both body and cap)

4 CONTRAINDICATIONS

- Hypersensitivity to methylphenidate or other components of methylphenidate hydrochloride extended-release capsules (LA). Hypersensitivity reactions, such as angioedema and anaphylactic reactions, have been reported in patients treated with methylphenidate [see Adverse Reactions (6.1)].
- Concomitant treatment with monoamine oxidase inhibitors (MAOIs), or within 14 days following discontinuation of treatment with an MAOI, because of the risk of hypertensive crises [s ee Drug Interactions (7.1)].

5 WARNINGS AND PRECAUTIONS

5.1 Potential for Abuse and Dependence

CNS stimulants, including methylphenidate hydrochloride extended-release capsules (LA), other methylphenidate-containing products, and amphetamines, have a high potential for abuse and dependence. Assess the risk of abuse prior to prescribing, and monitor for signs of abuse and dependence while on therapy [see Boxed Warning, Drug Abuse and Dependence (9.2, 9.3)].

5.2 Serious Cardiovascular Reactions

Sudden death, stroke, and myocardial infarction have been reported in adults with CNS-stimulant treatment at recommended doses. Sudden death has been reported in pediatric patients with structural cardiac abnormalities and other serious heart problems taking CNS stimulants at recommended doses for ADHD. Avoid use in patients with known structural cardiac abnormalities, cardiomyopathy, serious heart rhythm abnormalities, coronary artery disease, and other serious heart problems. Further evaluate patients who develop exertional chest pain, unexplained syncope, or arrhythmias during methylphenidate hydrochloride extended-release capsules (LA) treatment.

5.3 Blood Pressure and Heart Rate Increases

CNS stimulants cause an increase in blood pressure (mean increase approximately 2 to 4 mmHg) and heart rate (mean increase approximately 3 to 6 beats per minute). Individuals may have larger increases. Monitor all patients for hypertension and tachycardia.

5.4 Psychiatric Adverse Reactions

Exacerbation of Preexisting Psychosis

CNS stimulants may exacerbate symptoms of behavior disturbance and thought disorder in patients with a preexisting psychotic disorder.

Induction of a Manic Episode in Patients with Bipolar Disorder

CNS stimulants may induce a manic or mixed mood episode in patients. Prior to initiating treatment, screen patients for risk factors for developing a manic episode (e.g., comorbid or history of depressive symptoms or a family history of suicide, bipolar disorder, or depression).

New Psychotic or Manic Symptoms

CNS stimulants, at recommended doses, may cause psychotic or manic symptoms (e.g., hallucinations, delusional thinking, or mania) in patients without a prior history of psychotic illness or mania. If such symptoms occur, consider discontinuing methylphenidate hydrochloride extended-release capsules (LA). In a pooled analysis of multiple short-term, placebo-controlled studies of CNS stimulants, psychotic or manic symptoms occurred in approximately 0.1% of CNS stimulant-treated patients, compared to 0 in placebo-treated patients.

5.5 Priapism

Prolonged and painful erections, sometimes requiring surgical intervention, have been reported with methylphenidate products in both pediatric and adult patients. Priapism was not reported with drug initiation but developed after some time on the drug, often subsequent to an increase in dose. Priapism has also appeared during a period of drug withdrawal (drug holidays or during discontinuation). Patients who develop abnormally sustained or frequent and painful erections should seek immediate medical attention.

5.6 Peripheral Vasculopathy, Including Raynaud's Phenomenon

CNS Stimulants, including methylphenidate hydrochloride extended-release capsules (LA), used to treat ADHD are associated with peripheral vasculopathy, including Raynaud's phenomenon. Signs and symptoms are usually intermittent and mild; however, very rare sequelae include digital ulceration and/or soft tissue breakdown. Effects of peripheral vasculopathy, including Raynaud's phenomenon, were observed in post-marketing reports at different times and at therapeutic doses in all age groups throughout the course of treatment. Signs and symptoms generally improve after reduction in dose or discontinuation of drug. Careful observation for digital changes is necessary during treatment with ADHD stimulants. Further clinical evaluation (e.g., rheumatology referral) may be appropriate for certain patients.

5.7 Long-Term Suppression of Growth

CNS stimulants have been associated with weight loss and slowing of growth rate in pediatric patients.

Careful follow-up of weight and height in pediatric patients ages 7 to 10 years who were randomized to either methylphenidate or non-medication treatment groups over 14 months, as well as in naturalistic subgroups of newly methylphenidate-treated and non-medication treated patients over 36 months (to the ages of 10-13 years), suggests that consistently medicated pediatric patients (i.e., treatment for 7 days per week throughout the year) have a temporary slowing in growth rate (on average, a total of about 2 cm less growth in height and 2.7 kg less growth in weight over 3 years), without evidence of growth rebound during this period of development.

Closely monitor growth (weight and height) in pediatric patients treated with CNS stimulants, including methylphenidate hydrochloride extended-release capsules (LA). Patients who are not growing or gaining height or weight as expected may need to have their treatment interrupted.

6 ADVERSE REACTIONS

The following are discussed in more detail in other sections of the labeling:

- Abuse and Dependence [see Boxed Warning, Warnings and Precautions (5.1), Drug Abuse and Dependence (9.2, 9.3)]
- Known hypersensitivity to methylphenidate or other ingredients of methylphenidate hydrochloride extended-release capsules (LA) [see Contraindications (4)]
- Hypertensive crisis when used concomitantly with Monoamine Oxidase Inhibitors [see Contraindications (4), Drug Interactions (7.1)]
- Serious Cardiovascular Reactions [see Warnings and Precautions (5.2)]
- Blood Pressure and Heart Rate Increases [see Warnings and Precautions (5.3)]
- Psychiatric Adverse Reactions [see Warnings and Precautions (5.4)]
- Priapism [see Warnings and Precautions (5.5)]
- Peripheral Vasculopathy, Including Raynaud's Phenomenon [see Warnings and Precautions (5.6)]
- Long-Term Suppression of Growth [see Warnings and Precautions (5.7)]

6.1 Clinical Trial Experience

Because clinical trials are conducted under widely varying conditions, adverse reaction rates observed in the clinical trials of a drug cannot be directly compared to rates in the clinical trials of another drug and may not reflect the rates observed in practice.

The clinical program for methylphenidate hydrochloride extended-release capsules (LA) consisted of 6 studies: 2 controlled clinical studies conducted in children with ADHD aged 6 to 12 years and 4 clinical pharmacology studies conducted in healthy adult volunteers. These studies included a total of 256 subjects; 195 children with ADHD and 61 healthy adult volunteers. The subjects received methylphenidate hydrochloride extended-release capsules (LA) in doses of 10 to 40 mg per day. Safety of methylphenidate hydrochloride extended-release capsules (LA) was assessed by evaluating frequency and nature of adverse events, routine laboratory tests, vital signs, and body weight. A placebo-controlled, double-blind, parallel-group study was conducted to evaluate the efficacy and safety of methylphenidate hydrochloride extended-release capsules (LA) in children with ADHD aged 6 to 12 years. All subjects received methylphenidate hydrochloride extended-release capsules (LA) for up to 4 weeks, and had their dose optimally adjusted, prior to entering the double-blind phase of the trial. In the 2-week double-blind treatment phase of this study, patients received either placebo or methylphenidate hydrochloride extended-release capsules (LA) at their individually-titrated dose (range, 10 to 40 mg).

Adverse reactions with an incidence greater than 5% during the initial 4-week single-blind methylphenidate hydrochloride extended-release capsules (LA) titration period of this study were headache, insomnia, upper abdominal pain, appetite decreased, and anorexia.

Adverse reactions with an incidence greater than 2% among methylphenidate hydrochloride extended-release capsules (LA) -treated subjects, during the 2-week double-blind phase of the clinical study, are shown in Table 2:

Table 2: Adverse Reactions in Greater Than 2% Methylphenidate Hydrochloride Extended-Release Capsules (LA)-Treated Subjects in the 2-Week Double-Blind Phase
Preferred Term | Methylphenidate Hydrochloride Extended-Release Capsules (LA) N = 65 N (%) | Placebo N = 71 N (%)
Anorexia | 2 (3.1) | 0 (0.0)
Insomnia | 2 (3.1) | 0 (0.0)

Adverse Events Associated with Discontinuation of Treatment

In the 2-week double-blind treatment phase of a placebo-controlled parallel-group study in children with ADHD, one methylphenidate hydrochloride extended-release capsules (LA)-treated subject (1/65, 1.5%) discontinued due to an adverse event (depressed mood).

In the single-blind titration period of this study, subjects received methylphenidate hydrochloride extended-release capsules (LA) for up to 4 weeks. During this period a total of 6 subjects (6/161, 3.7%) discontinued due to adverse events. The adverse events leading to discontinuation were anger (2 patients), hypomania, anxiety, depressed mood, fatigue, migraine, and lethargy.

6.2 Postmarketing Experience

The following adverse reactions have been identified during the post approval use of methylphenidate products. Because these reactions were reported voluntarily from a population of uncertain size, it is not always possible to estimate their frequency reliably or to establish a causal relationship to drug exposure.

Adverse Reactions Reported With Methylphenidate Hydrochloride Tablets, Methylphenidate Hydrochloride Extended-Release Tablets, and Methylphenidate Hydrochloride Extended- Release Capsules (LA)

Infections and Infestations:nasopharyngitis

Blood and the Lymphatic System Disorders:leukopenia, thrombocytopenia, anemia

Immune System Disorders:hypersensitivity reactions, including angioedema and anaphylaxis

Metabolism and Nutrition Disorders:decreased appetite, reduced weight gain, and suppression of growth during prolonged use in children

Psychiatric Disorders:insomnia, anxiety, restlessness, agitation, psychosis (sometimes with visual and tactile hallucinations), depressed mood

Nervous System Disorders:headache, dizziness, tremor, dyskinesia, including choreoathetoid movements, drowsiness, convulsions, cerebrovascular disorders (including vasculitis, cerebral hemorrhages and cerebrovascular accidents), serotonin syndrome in combination with serotonergic drugs

Eye Disorders:blurred vision, difficulties in visual accommodation

Cardiac Disorders:tachycardia, palpitations, increased blood pressure, arrhythmias, angina pectoris

Respiratory, Thoracic, and Mediastinal Disorders:cough

Gastrointestinal Disorders:dry mouth, nausea, vomiting, abdominal pain, dyspepsia

Hepatobiliary Disorders:abnormal liver function, ranging from transaminase elevation to severe hepatic injury

Skin and Subcutaneous Tissue Disorders:hyperhidrosis, pruritus, urticaria, exfoliative dermatitis, scalp hair loss, erythema multiforme rash, thrombocytopenic purpura

Musculoskeletal and connective tissue disorders:arthralgia, muscle cramps, rhabdomyolysis

Investigations:weight loss (adult ADHD patients)

Adverse Reactions Reported with Other Methylphenidate-Containing Products

The list below shows adverse reactions not listed with methylphenidate hydrochloride tablets, methylphenidate hydrochloride extended-release tablets, or methylphenidate hydrochloride extended-release capsules (LA) formulations that have been reported with other methylphenidate-containing products.

Blood and Lymphatic Disorders: pancytopenia

Immune System Disorders:hypersensitivity reactions, such as auricular swelling, bullous conditions, eruptions, exanthemas

Psychiatric Disorders:affect lability, mania, disorientation, libido changes,

Nervous System Disorders:migraine

Eye Disorders:diplopia, mydriasis

Cardiac Disorders:sudden cardiac death, myocardial infarction, bradycardia, extrasystole

Vascular Disorders:peripheral coldness, Raynaud's phenomenon

Respiratory, Thoracic, and Mediastinal Disorders:pharyngolaryngeal pain, dyspnea

Gastrointestinal Disorders:diarrhea, constipation

Skin and Subcutaneous Tissue Disorders:angioneurotic edema, erythema, fixed drug eruption

Musculoskeletal, Connective Tissue, and Bone Disorders:myalgia, muscle twitching

Renal and Urinary Disorders:hematuria

Reproductive System and Breast Disorders:gynecomastia

General Disorders:fatigue, hyperpyrexia

Urogenital Disorders:priapism

7 DRUG INTERACTIONS

7.1 Clinically Important Drug Interactions With Methylphenidate Hydrochloride Extended-Release Capsules (LA)

Table 3 presents clinically important drug interactions with methylphenidate hydrochloride extended-release capsules (LA)

Table 3: Clinically Important Drug Interactions With Methylphenidate Hydrochloride Extended-Release Capsules (LA)
Monoamine Oxidase Inhibitors (MAOI)
Clinical Impact | Concomitant use of MAOIs and CNS stimulants, including methylphenidate hydrochloride extended-release capsules (LA), can cause hypertensive crisis. Potential outcomes include death, stroke, myocardial infarction, aortic dissection, ophthalmological complications, eclampsia, pulmonary edema, and renal failure [see Contraindications (4)] .
Intervention | Concomitant use of methylphenidate hydrochloride extended-release capsules (LA) with MAOIs or within 14 days after discontinuing MAOI treatment is contraindicated.
Examples | selegiline, tranylcypromine, isocarboxazid, phenelzine, linezolid, methylene blue
Antihypertensive Drugs
Clinical Impact | Methylphenidate hydrochloride extended-release capsules (LA) may decrease the effectiveness of drugs used to treat hypertension [see Warnings and Precautions (5.3)] .
Intervention | Monitor blood pressure and adjust the dosage of the antihypertensive drug as needed.
Examples | Potassium-sparing and thiazide diuretics, calcium channel blockers, angiotensin-converting-enzyme (ACE) inhibitors, angiotensin II receptor blockers (ARBs), beta blockers, centrally acting alpha-2 receptor agonists.
Halogenated Anesthetics
Clinical Impact | Concomitant use of halogenated anesthetics and methylphenidate hydrochloride extended-release capsules (LA) may increase the risk of sudden blood pressure and heart rate increase during surgery.
Intervention | Avoid use of methylphenidate hydrochloride extended-release capsules (LA) in patients being treated with anesthetics on the day of surgery.
Examples | halothane, isoflurane, enflurane, desflurane, sevoflurane
Risperidone
Clinical Impact | Combined use of methylphenidate with risperidone when there is a change, whether an increase or decrease, in dosage of either or both medications, may increase the risk of extrapyramidal symptoms (EPS)
Intervention | Monitor for signs of EPS

8 USE IN SPECIFIC POPULATIONS

8.1 Pregnancy

Pregnancy Exposure Registry

There is a pregnancy exposure registry that monitors pregnancy outcomes in women exposed to ADHD medications, including methylphenidate hydrochloride extended-release capsules (LA) during pregnancy. Healthcare providers are encouraged to register patients by calling the National Pregnancy registry for ADHD medications at 1-866-961-2388 or visit https://womensmentalhealth.org/adhd-medications/.

Risk Summary

Published studies and postmarketing reports on methylphenidate use during pregnancy have not identified a drug-associated risk of major birth defects, miscarriage or adverse maternal or fetal outcomes. There may be risks to the fetus associated with the use of CNS stimulants use during pregnancy (see Clinical Considerations) . No effects on morphological development were observed in embryo-fetal development studies with oral administration of methylphenidate to pregnant rats and rabbits during organogenesis at doses up to 10 and 15 times, respectively, the maximum recommended human dose (MRHD) of 60 mg/day given to adolescents on a mg/m^2basis. However, spina bifida was observed in rabbits at a dose 52 times the MRHD given to adolescents. A decrease in pup body weight was observed in a pre- and post-natal development study with oral administration of methylphenidate to rats throughout pregnancy and lactation at doses 6 times the MRHD given to adolescents (see Data) .

The estimated background risk of major birth defects and miscarriage for the indicated population is unknown. All pregnancies have a background risk of birth defect, loss, or other adverse outcomes. In the U.S. general population, the estimated background risk of major birth defects and miscarriage in clinically recognized pregnancies is 2% to 4% and 15% to 20%, respectively.

Clinical Considerations

Fetal/Neonatal Adverse Reactions

CNS stimulants, such as methylphenidate hydrochloride extended-release capsules (LA), can cause vasoconstriction and thereby decrease placental perfusion. No fetal and/or neonatal adverse reactions have been reported with the use of therapeutic doses of methylphenidate during pregnancy; however, premature delivery and low birth weight infants have been reported in amphetamine-dependent mothers.

Data

Animal Data

In embryo-fetal development studies conducted in rats and rabbits, methylphenidate was administered orally at doses of up to 75 and 200 mg/kg/day, respectively, during the period of organogenesis. Malformations (increased incidence of fetal spina bifida) were observed in rabbits at the highest dose, which is approximately 52 times the MRHD of 60 mg/day given to adolescents on a mg/m^2basis. The no effect level for embryo-fetal development in rabbits was 60 mg/kg/day (15 times the MRHD given to adolescents on a mg/m^2basis). There was no evidence of morphological development effects in rats, although increased incidences of fetal skeletal variations were seen at the highest dose level (10 times the MRHD of 60 mg/day given to adolescents on a mg/m^2basis), which was also maternally toxic. The no effect level for embryo-fetal development in rats was 25 mg/kg/day (3 times the MRHD on a mg/m^2basis). When methylphenidate was administered to rats throughout pregnancy and lactation at doses of up to 45 mg/kg/day, offspring body weight gain was decreased at the highest dose (6 times the MRHD of 60 mg/day given to adolescents on a mg/m^2basis), but no other effects on postnatal development were observed. The no effect level for pre- and postnatal development in rats was 15 mg/kg/day (~2 times the MRHD given to adolescents on a mg/m^2basis).

8.2 Lactation

Risk Summary

Limited published literature, based on milk sampling from seven mothers reports that methylphenidate is present in human milk, which resulted in infant doses of 0.16% to 0.7% of the maternal weight-adjusted dosage and a milk/plasma ratio ranging between 1.1 and 2.7. There are no reports of adverse effects on the breastfed infant and no effects on milk production. Long-term neurodevelopmental effects on infants from stimulant exposure are unknown. The developmental and health benefits of breastfeeding should be considered along with the mother's clinical need for methylphenidate hydrochloride extended-release capsules (LA) and any potential adverse effects on the breastfed infant from methylphenidate hydrochloride extended-release capsules (LA) or from the underlying maternal condition.

Clinical Considerations

Monitor breastfeeding infants for adverse reactions, such as agitation, insomnia, anorexia, and reduced weight gain.

8.4 Pediatric Use

The safety and effectiveness of methylphenidate hydrochloride extended-release capsules (LA) for the treatment of ADHD have been established in pediatric patients 6 to 12 years.

The safety and effectiveness of methylphenidate hydrochloride extended-release capsules (LA) in pediatric patients less than 6 years have not been established. The long-term efficacy of methylphenidate hydrochloride extended-release capsules (LA) in pediatric patients has not been established.

Long-Term Suppression of Growth

Growth should be monitored during treatment with stimulants, including methylphenidate hydrochloride extended release-capsules (LA). Pediatric patients who are not growing or gaining weight as expected may need to have their treatment interrupted [see Warnings and Precautions (5.7)] .

Juvenile Animal Toxicity Data

Rats treated with methylphenidate early in the postnatal period through sexual maturation demonstrated a decrease in spontaneous locomotor activity in adulthood. A deficit in acquisition of a specific learning task was observed in females only. The doses at which these findings were observed are at least 4 times the MRHD of 60 mg/day given to children on a mg/m^2basis.

In a study conducted in young rats, methylphenidate was administered orally at doses of up to 100 mg/kg/day for 9 weeks, starting early in the postnatal period (postnatal Day 7) and continuing through sexual maturity (postnatal Week 10). When these animals were tested as adults (postnatal Weeks 13 to 14), decreased spontaneous locomotor activity was observed in males and females previously treated with 50 mg/kg/day (approximately 4 times the MRHD of 60 mg/day given to children on a mg/m^2basis) or greater, and a deficit in the acquisition of a specific learning task was seen in females exposed to the highest dose (8 times the MRHD given to children on a mg/m^2basis). The no effect level for juvenile neurobehavioral development in rats was 5 mg/kg/day (approximately 0.5 times the MRHD given to children on a mg/m^2basis). The clinical significance of the long-term behavioral effects observed in rats is unknown.

8.5 Geriatric Use

Methylphenidate hydrochloride extended-release capsules (LA) has not been studied in the geriatric population.

9 DRUG ABUSE AND DEPENDENCE

9.1 Controlled Substance

Methylphenidate hydrochloride extended-release capsules (LA) contains methylphenidate hydrochloride, a Schedule II controlled substance.

9.2 Abuse

CNS stimulants, including methylphenidate hydrochloride extended-release capsules (LA), have a high potential for abuse. Abuse is characterized by impaired control over drug use despite harm, and craving.

Signs and symptoms of CNS stimulant abuse include increased heart rate, respiratory rate, blood pressure, and/or sweating, dilated pupils, hyperactivity, restlessness, insomnia, decreased appetite, loss of coordination, tremors, flushed skin, vomiting, and/or abdominal pain. Anxiety, psychosis, hostility, aggression, and suicidal or homicidal ideation have also been observed. Abusers of CNS stimulants may chew, snort, inject, or use other unapproved routes of administration which may result in overdose and death [see Overdosage (10)] .

To reduce the abuse of CNS stimulants, including methylphenidate hydrochloride extended-release capsules (LA), assess the risk of abuse prior to prescribing. After prescribing, keep careful prescription records, educate patients and their families about abuse and on proper storage and disposal of CNS stimulants [see How Supplied/Storage and Handling (16)] , monitor for signs of abuse while on therapy, and reevaluate the need for methylphenidate hydrochloride tablets and methylphenidate hydrochloride extended-release tablets use.

9.3 Dependence

Tolerance

Tolerance (a state of adaptation in which exposure to a drug results in a reduction of the drug's desired and/or undesired effects over time) can occur during chronic therapy with CNS stimulants, including methylphenidate hydrochloride extended-release capsules (LA).

Dependence

Physical dependence (which is manifested by a withdrawal syndrome produced by abrupt cessation, rapid dose reduction, or administration of an antagonist) may occur in patients treated with CNS stimulants, including methylphenidate hydrochloride tablets and methylphenidate hydrochloride extended-release tablets. Withdrawal symptoms after abrupt cessation following prolonged high-dosage administration of CNS stimulants include dysphoric mood; fatigue; vivid, unpleasant dreams; insomnia or hypersomnia; increased appetite; and psychomotor retardation or agitation.

10 OVERDOSAGE

Human Experience

Signs and symptoms of acute overdosage, resulting principally from overstimulation of the central nervous system and from excessive sympathomimetic effects, may include the following: nausea, vomiting, diarrhea, restlessness, anxiety, agitation, tremors, hyperreflexia, muscle twitching, convulsions (which may be followed by coma), euphoria, confusion, hallucinations, delirium, sweating, flushing, headache, hyperpyrexia, tachycardia, palpitations, cardiac arrhythmias, hypertension, hypotension, tachypnea, mydriasis, dryness of mucous membranes, and rhabdomyolysis.

Overdose Management

Consult with a Certified Poison Control Center (1-800-222-1222) for the latest recommendations.

11 DESCRIPTION

Methylphenidate hydrochloride extended-release capsules (LA) contains methylphenidate hydrochloride USP, a CNS stimulant.

Methylphenidate hydrochloride extended-release capsules (LA) is an extended-release formulation of methylphenidate for oral administration with a bi-modal release profile. Each bead-filled methylphenidate hydrochloride extended-release capsule (LA) contains half the dose as immediate-release beads and half as enteric-coated beads, thus providing an immediate release of methylphenidate and a second delayed release of methylphenidate.

The active substance in methylphenidate hydrochloride extended-release capsules (LA) is methyl α-phenyl-2-piperidineacetate hydrochloride, and its structural formula is

Methylphenidate hydrochloride USP is a white, odorless, fine crystalline powder. Its solutions are acid to litmus. It is freely soluble in water and in methanol, soluble in alcohol, and slightly soluble in chloroform and in acetone. Its molecular weight is 269.77 g/mol.

Inactive ingredients:Sugar spheres (which contain sucrose and starch (corn)), hypromellose, cellulose acetate butyrate, hypromellose acetate succinate, acetyltributyl citrate, acetone, talc, and purified water. Opaque gelatin capsules contain: titanium dioxide and gelatin. The 10mg capsule contains FD&C Green#3, FD&C#40, and FD&C Yellow #6. The 30 and 40 mg capsules contain D&C Red #28 and FD&C Blue #1. The 60 mg capsules contain iron oxide yellow and sodium lauryl sulfate. The capsules are imprinted with black ink which contains black iron oxide, shellac and potassium hydroxide. The 60 mg black imprinting ink also contains ammonium hydroxide and propylene glycol.

12 CLINICAL PHARMACOLOGY

12.1 Mechanism of Action

Methylphenidate hydrochloride is a CNS stimulant. The mode of therapeutic action in ADHD is not known.

12.2 Pharmacodynamics

Methylphenidate is a racemic mixture comprised of the d-and l-threoenantiomers. The d-threoenantiomer is more pharmacologically active than the l-threoenantiomer. Methylphenidate blocks the reuptake of norepinephrine and dopamine into the presynaptic neuron and increase the release of these monoamines into the extraneuronal space.

Cardiac Electrophysiology

A formal QT study has not been conducted in patients taking methylphenidate hydrochloride extended-release capsules (LA).

The effect of dexmethylphenidate, the pharmacologically active d-enantiomer of methylphenidate hydrochloride tablets, on the QT interval was evaluated in a double-blind, placebo- and open-label active (moxifloxacin)-controlled study following single doses of dexmethylphenidate XR 40mg (maximum recommended adult total daily dosage) in 75 healthy volunteers. Electrocardiograms were collected up to 12 hours postdose. Frederica's method for heart rate correction was employed to derive the corrected QT interval (QTcF). The maximum mean prolongation of QTcF intervals was less than 5 ms, and the upper limit of the 90% confidence interval was below 10 ms for all time matched comparisons versus placebo. This was below the threshold of clinical concern and there was no evident-exposure response relationship.

12.3 Pharmacokinetics

Methylphenidate hydrochloride extended-release capsules (LA) produces a bi-modal plasma concentration-time profile (i.e., 2 distinct peaks approximately 4 hours apart) when administered orally to children diagnosed with ADHD and healthy adults.

No accumulation of methylphenidate is expected following multiple once daily oral dosing with methylphenidate hydrochloride extended-release capsules (LA), however, there is a slight upward trend in the methylphenidate area under the curve and peak plasma concentrations (Cmax1and Cmax2) after oral administration of methylphenidate hydrochloride extended-release capsules (LA) 20 mg and 40 mg to adults.

Absorption

The absolute oral bioavailability of methylphenidate in children was 22 ± 8% for d-methylphenidate and 5 ± 3% for l- methylphenidate. The relative bioavailability of methylphenidate hydrochloride extended-release capsules (LA) given once daily is comparable to the same total dose of methylphenidate hydrochloride tablets given in 2 doses 4 hours apart in both children and adults.

The initial rate of absorption for methylphenidate hydrochloride extended-release capsules (LA) is similar to that of methylphenidate hydrochloride tablets as shown by the similar rate parameters between the 2 formulations, i.e., initial lag time (Tlag), first peak concentration (Cmax1), and time to the first peak (Tmax1), which is reached in 1 to 3 hours. The mean time to the interpeak minimum (Tminip), and time to the second peak (Tmax2) are also similar for methylphenidate hydrochloride extended-release capsules (LA) given once daily and methylphenidate hydrochloride tablets given in 2 doses 4 hours apart (see Figure 1and Table 1), although the ranges observed are greater for methylphenidate hydrochloride extended-release capsules (LA).

Methylphenidate hydrochloride extended-release capsules (LA) given once daily exhibits a lower second peak concentration (Cmax2), higher interpeak minimum concentrations (Cminip), and less peak and trough fluctuations than methylphenidate hydrochloride tablets given in 2 doses given 4 hours apart. This is due to an earlier onset and more prolonged absorption from the delayed-release beads (see Figure 1and Table 4).

Figure 1: Mean Plasma Concentration Time-profile of Methylphenidate After a Single Dose of Methylphenidate Hydrochloride Extended-Release Capsule (LA) 40 mg and Methylphenidate Hydrochloride Tablets 20 mg Given in Two Doses 4 Hours Apart

Table 4: Mean ± SD and Range of Pharmacokinetic Parameters of Methylphenidate After a Single Dose of Methylphenidate Hydrochloride Extended-Release Capsules (LA) and Methylphenidate Hydrochloride Tablets Given in Two Doses 4 Hours Apart
Population | Children |  | Adult Males
Formulation | Methylphenidate Hydrochloride Tablets | Methylphenidate Hydrochloride Extended-Release Capsules (LA) | Methylphenidate Hydrochloride Tablets | Methylphenidate Hydrochloride Extended-Release Capsules (LA)
Dose N | 10 mg & 10 mg 21 | 20 mg 18 | 10 mg & 10 mg 9 | 20 mg 8
Tlag(h) | 0.24 ± 0.44 0 – 1 | 0.28 ± 0.46 0 - 1 | 1.0 ± 0.5 0.7 - 1.3 | 0.7 ± 0.2 0.3 - 1.0
Tmax1(h) | 1.8 ± 0.6 1 – 3 | 2.0 ± 0.8 1 - 3 | 1.9 ± 0.4 1.3 - 2.7 | 2.0 ± 0.9 1.3 - 4.0
Cmax1(ng/mL) | 10.2 ± 4.2 4.2 - 20.2 | 10.3 ± 5.1 5.5 - 26.6 | 4.3 ± 2.3 1.8 - 7.5 | 5.3 ± 0.9 3.8 - 6.9
Tminip(h) | 4.0 ± 0.2 4 – 5 | 4.5 ± 1.2 2 - 6 | 3.8 ± 0.4 3.3 - 4.3 | 3.6 ± 0.6 2.7 - 4.3
Cminip(ng/mL) | 5.8 ± 2.7 3.1 - 14.4 | 6.1 ± 4.1 2.9 - 21.0 | 1.2 ± 1.4 0.0 - 3.7 | 3.0 ± 0.8 1.7 - 4.0
Tmax2(h) | 5.6 ± 0.7 5 – 8 | 6.6 ± 1.5 5 - 11 | 5.9 ± 0.5 5.0 - 6.5 | 5.5 ± 0.8 4.3 - 6.5
Cmax2(ng/mL) | 15.3 ± 7.0 6.2 - 32.8 | 10.2 ± 5.9 4.5 - 31.1 | 5.3 ± 1.4 3.6 - 7.2 | 6.2 ± 1.6 3.9 - 8.3
AUC(0-∞) (ng/mL × h-1) | 102.4 ± 54.6 40.5 - 261.6 | 86.6 ± 64.0 [N = 15] 43.3 - 301.44 | 37.8 ± 21.9 14.3 - 85.3 | 45.8 ± 10.0 34.0 - 61.6
t1/2(h) | 2.5 ± 0.8 1.8 - 5.3 | 2.4 ± 0.7 1.5 - 4.0 | 3.5 ± 1.9 1.3 - 7.7 | 3.3 ± 0.4 3.0 - 4.2

Effect of Food

Administration times relative to meals and meal composition may need to be individually titrated.

When methylphenidate hydrochloride extended-release capsules (LA) was administered with a high fat breakfast to adults, methylphenidate hydrochloride extended-release capsules (LA) had a longer lag time until absorption began and variable delays in the time until the first peak concentration, the time until the interpeak minimum, and the time until the second peak. The first peak concentration and the extent of absorption were unchanged after food relative to the fasting state, although the second peak was approximately 25% lower. The effect of a high fat lunch was not examined.

There were no differences in the pharmacokinetics of methylphenidate hydrochloride extended-release capsules (LA) when administered with applesauce, compared to administration in the fasting condition. There is no evidence of dose dumping in the presence or absence of food.

Effect of Alcohol

An in vitrostudy was conducted to explore the effect of alcohol on the release characteristics of methylphenidate from the methylphenidate hydrochloride extended-release capsules (LA) 40 mg dosage form. At an alcohol concentration of 40% there was a 98% release of methylphenidate in the first hour. The results with the 40 mg capsule are considered to be representative of the other available capsule strengths.

Distribution

Binding to plasma proteins is low (10% to 33%). The volume of distribution was 2.65 ± 1.11 L/kg for d- methylphenidate and 1.80 ± 0.91 L/kg for l-methylphenidate.

Elimination

The systemic clearance is 0.40 ± 0.12 L/h/kg for d-methylphenidate and 0.73 ± 0.28 L/h/kg for l-methylphenidate. In studies with methylphenidate hydrochloride extended-release capsules (LA) and methylphenidate hydrochloride tablets in adults, methylphenidate from methylphenidate hydrochloride tablets is eliminated from plasma with an average half-life of about 3.5 hours, (range, 1.3 to 7.7 hours). In children the average half-life is about 2.5 hours, with a range of about 1.5 to 5.0 hours. The rapid half-life in both children and adults may result in un-measurable concentrations between the morning and mid-day doses with methylphenidate hydrochloride tablets. No accumulation of methylphenidate is expected following multiple once a day oral dosing with methylphenidate hydrochloride extended-release capsules (LA). The half-life of ritalinic acid is about 3 to 4 hours.

Metabolism

The absolute oral bioavailability of methylphenidate in children was 22 ± 8% for d-methylphenidate and 5 ± 3% for l- methylphenidate, suggesting pronounced presystemic metabolism. Biotransformation of methylphenidate by the carboxylesterase CES1A1 is rapid and extensive leading to the main, de-esterified metabolite α-phenyl-2-piperidine acetic acid (ritalinic acid), which has little or no pharmacologic activity. Only small amounts of hydroxylated metabolites (e.g., hydroxymethylphenidate and hydroxyritalinic acid) are detectable in plasma. Therapeutic activity is principally due to the parent compound.

Excretion

After oral administration of an immediate release formulation of methylphenidate, 78% to 97% of the dose is excreted in the urine and 1% to 3% in the feces in the form of metabolites within 48 to 96 hours. Only small quantities (less than 1%) of unchanged methylphenidate appear in the urine. Most of the dose is excreted in the urine as ritalinic acid (60% to 86%), the remainder being accounted for by minor metabolite.

Studies in Specific Populations

Male and Female Patients

There were no apparent gender differences in the pharmacokinetics of methylphenidate between healthy male and female adults when administered methylphenidate hydrochloride extended-release capsules (LA).

Racial or Ethnic Groups

There is insufficient experience with the use of methylphenidate hydrochloride extended-release capsules (LA) to detect ethnic variations in pharmacokinetics.

Pediatric Patients

The pharmacokinetics of methylphenidate hydrochloride extended-release capsules (LA) was examined in 18 children with ADHD between 7 and 12 years of age. Fifteen of these children were between 10 and 12 years of age. The time until the between peak minimum, and the time until the second peak were delayed and more variable in children compared to adults. After a 20-mg dose of methylphenidate hydrochloride extended-release capsules (LA), concentrations in children were approximately twice the concentrations observed in 18 to 35 year old adults. This higher exposure is almost completely due to the smaller body size and total volume of distribution in children, as apparent clearance normalized to body weight is independent of age.

Patients with Renal Impairment

Methylphenidate hydrochloride extended-release capsules (LA) has not been studied in renally-impaired patients. Renal impairment is expected to have minimal effect on the pharmacokinetics of methylphenidate since less than 1% of a radiolabeled dose is excreted in the urine as unchanged compound, and the major metabolite (ritalinic acid), has little or no pharmacologic activity.

Patients with Hepatic Impairment

Methylphenidate hydrochloride extended-release capsules (LA) has not been studied in patients with hepatic impairment. Hepatic impairment is expected to have minimal effect on the pharmacokinetics of methylphenidate since it is metabolized primarily to ritalinic acid by nonmicrosomal hydrolytic esterases that are widely distributed throughout the body.

13 NONCLINICAL TOXICOLOGY

13.1 Carcinogenesis, Mutagenesis, and Impairment of Fertility

Carcinogenesis

In a lifetime carcinogenicity study carried out in B6C3F1 mice, methylphenidate caused an increase in hepatocellular adenomas, and in males only, an increase in hepatoblastomas at a daily dose of approximately 60 mg/kg/day. This dose is approximately 2 times the (MRHD) of 60 mg/day given to children on a mg/m^2basis. Hepatoblastoma is a relatively rare rodent malignant tumor type. There was no increase in total malignant hepatic tumors. The mouse strain used is sensitive to the development of hepatic tumors, and the significance of these results to humans is unknown.

Methylphenidate did not cause any increase in tumors in a lifetime carcinogenicity study carried out in F344 rats; the highest dose used was approximately 45 mg/kg/day, which is approximately 4 times the MRHD (children) on a mg/m^2basis.

In a 24-week carcinogenicity study in the transgenic mouse strain p53+/-, which is sensitive to genotoxic carcinogens, there was no evidence of carcinogenicity. Male and female mice were fed diets containing the same concentration of methylphenidate as in the lifetime carcinogenicity study; the high-dose groups were exposed to 60 to 74 mg/kg/day of methylphenidate.

Mutagenesis

Methylphenidate was not mutagenic in the in vitroAmes reverse mutation assay, in the in vitromouse lymphoma cell forward mutation assay, or in the in vitrochromosomal aberration assay using human lymphocytes. Sister chromatid exchanges and chromosome aberrations were increased, indicative of a weak clastogenic response, in an in vitroassay in cultured Chinese Hamster Ovary cells. Methylphenidate was negative in vivoin males and females in the mouse bone marrow micronucleus assay.

Impairment of Fertility

Methylphenidate did not impair fertility in male or female mice that were fed diets containing the drug in an 18-week continuous breeding study. The study was conducted at doses up to 160 mg/kg/day, approximately 10 times the maximum recommended dose of 60 mg/day given to adolescents on a mg/m^2basis.

14 CLINICAL STUDIES

14.1 Children and Adolescents

Methylphenidate hydrochloride extended-release capsules (LA) was evaluated in a randomized, double-blind, placebo-controlled, parallel group clinical study in which 134 children, ages 6 to 12, with DSM-IV diagnoses of ADHD received a single morning dose of methylphenidate hydrochloride extended-release capsules (LA)in the range of 10 to 40 mg/day, or placebo, for up to 2 weeks. The doses used were the optimal doses established in a previous individual dose titration phase. In that titration phase, 53 of 164 patients (32%) started on a daily dose of 10 mg and 111 of 164 patients (68%) started on a daily dose of 20 mg or higher. The patient's regular schoolteacher completed the Conners ADHD/DSM-IV Scale for Teachers (CADS-T) at baseline and the end of each week. The CADS-T assesses symptoms of hyperactivity and inattention. The change from baseline of the (CADS-T) scores during the last week of treatment was analyzed as the primary efficacy parameter. Patients treated with methylphenidate hydrochloride extended-release capsules (LA) showed a statistically significant improvement in symptom scores from baseline [Mean (final score - baseline) = -10.7 points)] over patients who received placebo [Mean (final score - baseline) = +2.8 points ]. The lower the final score on the CADS-T scale from baseline, the less severe the disease is. This demonstrates that a single morning dose of methylphenidate hydrochloride extended-release capsules (LA) exerts a treatment effect in ADHD.

Figure 2: CADS-T Total Subscale - Mean Change From Baseline*

16 HOW SUPPLIED/STORAGE AND HANDLING

10 mg white/light green capsules (imprinted mayne 609 on both the body and the cap)

Bottles of 100 | NDC 51862-609-01

20 mg white/white capsules (imprinted mayne 610 on both the body and cap

Bottles of 100 | NDC 51862-610-01

30 mg white/light blue capsules (imprinted mayne 611 on both the body and cap

Bottles of 100 | NDC 51862-611-01

40 mg white/dark blue capsules (imprinted mayne 612 on both the body and cap)

Bottles of 100 | NDC 51862-612-01

60 mg light yellow/dark yellow capsules (imprinted mayne 614 on both the body and cap)

Bottles of 30 | NDC 51862-614-30

STORAGE AND HANDLING

Store at 20°C to 25°C (68°F to 77°F); excursions permitted between 15°C to 30°C (59°F and 86°F). [See USP controlled room temperature].

Dispense in tight container (USP).

Disposal

Comply with local laws and regulations on drug disposal of CNS stimulants. Dispose of remaining, unused, or expired methylphenidate hydrochloride extended-release capsules (LA) by a medicine takeback program or by an authorized collector registered with the Drug Enforcement Administration. If no take-back program or authorized collector is available, mix methylphenidate hydrochloride extended-release capsules (LA) with an undesirable, nontoxic substance to make it less appealing to children and pets. Place the mixture in a container, such as a sealed plastic bag and discard methylphenidate hydrochloride extended-release capsules (LA) in the household trash.

17 PATIENT COUNSELING INFORMATION

Advise the patient to read the FDA-approved patient labeling (Medication Guide)

Controlled Substance Status/High Potential for Abuse and Dependence

Advise patients that methylphenidate hydrochloride extended-release capsules (LA) is a controlled substance, and it can be abused and lead to dependence. Instruct patients that they should not give methylphenidate hydrochloride extended-release capsules (LA) to anyone else. Advise patients to store methylphenidate hydrochloride extended-release capsules (LA) in a safe place, preferably locked, to prevent abuse. Advise patients to comply with laws and regulations on drug disposal. Advise patients to dispose of remaining, unused, or expired methylphenidate hydrochloride extended-release capsules (LA) by a medicine take-back program if available [see Boxed Warning, Warnings and Precautions (5.1), Drug Abuse and Dependence (9.1, 9.2, 9.3), How Supplied/Storage and Handling (16)] .

Serious Cardiovascular Risks

Advise patients that there is a potential serious cardiovascular risk, including sudden death, myocardial infarction, stroke, and hypertension with methylphenidate hydrochloride extended-release capsules (LA) use. Instruct patients to contact a healthcare provider immediately if they develop symptoms, such as exertional chest pain, unexplained syncope, or other symptoms suggestive of cardiac disease [see Warnings and Precautions (5.2)].

Blood Pressure and Heart Rate Increases

Instruct patients that methylphenidate hydrochloride extended-release capsules (LA) can cause elevations of their blood pressure and pulse rate [see Warnings and Precautions (5.3)] .

Psychiatric Risks

Advise patients that methylphenidate hydrochloride extended-release capsules (LA), at recommended doses, can cause psychotic or manic symptoms, even in patients without prior history of psychotic symptoms or mania [see Warnings and Precautions (5.4)].

Priapism

Advise patients of the possibility of painful or prolonged penile erections (priapism). Instruct them to seek immediate medical attention in the event of priapism [see Warnings and Precautions (5.5)] .

Circulation Problems in Fingers and Toes [Peripheral Vasculopathy, Including Raynaud's Phenomenon]

Instruct patients beginning treatment with methylphenidate hydrochloride extended-release capsules (LA) about the risk of peripheral vasculopathy, including Raynaud's phenomenon, and associated signs and symptoms: fingers or toes may feel numb, cool, painful, and/or may change color from pale, to blue, to red. Instruct patients to report to their physician any new numbness, pain, skin color change, or sensitivity to temperature in fingers or toes.

Instruct patients to call their physician immediately with any signs of unexplained wounds appearing on fingers or toes while taking methylphenidate hydrochloride extended-release capsules (LA). Further clinical evaluation (e.g., rheumatology referral) may be appropriate for certain patients [see Warnings and Precautions (5.6)] .

Suppression of Growth

Advise patients that methylphenidate hydrochloride extended-release capsules (LA) may cause slowing of growth and weight loss [see Warnings and Precautions (5.7)].

Alcohol Effect

Advise patients to avoid alcohol while taking methylphenidate hydrochloride extended-release capsules (LA). Consumption of alcohol while taking methylphenidate hydrochloride extended-release capsules (LA) may result in a more rapid release of the dose of methylphenidate [see Clinical Pharmacology (12.3)] .

Pregnancy Registry

Advise patients that there is a pregnancy exposure registry that monitors pregnancy outcomes in patients exposed to methylphenidate hydrochloride extended-release capsules (LA) during pregnancy [see Use in Specific Populations (8.1)] .

Distributed by:
Mayne Pharma
Raleigh, NC 27609

AB7678

MEDICATION GUIDE
Methylphenidate Hydrochloride (METH-il-FEN-i-date HYE-droe-KLOR-ide)
Extended-Release Capsules (LA) CII

What is the most important information I should know about methylphenidate hydrochloride extended-release capsules (LA)?
Methylphenidate hydrochloride extended-release capsules (LA) is a federal controlled substance (CII) because it can be abused or lead to dependence. Keep methylphenidate hydrochloride extended-release capsules (LA) in a safe place to prevent misuse and abuse. Selling or giving away methylphenidate hydrochloride extended-release capsules (LA) may harm others, and is against the law. Tell your doctor if you or your child have ever abused or been dependent on alcohol, prescription medicines or street drugs.
The following have been reported with use of methylphenidate hydrochloride and other stimulant medicines.
1. Heart-related problems:

- sudden death in patients who have heart problems or heart defects
- stroke and heart attack in adults
- increased blood pressure and heart rate

Tell your doctor if you or your child have any heart problems, heart defects, high blood pressure, or a family history of these problems.
Your doctor should check you or your child carefully for heart problems before starting methylphenidate hydrochloride extended-release capsules (LA).
Your doctor should check your or your child's blood pressure and heart rate regularly during treatment with methylphenidate hydrochloride extended-release capsules (LA).
Call your doctor right away if you or your child has any signs of heart problems, such as chest pain, shortness of breath, or fainting while taking methylphenidate hydrochloride extended-release capsules (LA).
2. Mental (psychiatric) problems:
All Patients

- new or worse behavior and thought problems
- new or worse bipolar illness
- new or worse aggressive behavior or hostility
- new psychotic symptoms (such as hearing voices, believing things that are not true, are suspicious) or new manic symptoms

Tell your doctor about any mental problems you or your child have, or about a family history of suicide, bipolar illness, or depression.
Call your doctor right away if you or your child have any new or worsening mental symptoms or problems while taking methylphenidate hydrochloride extended-release capsules (LA), especially seeing or hearing things that are not real, believing things that are not real, or are suspicious.

What are methylphenidate hydrochloride extended-release capsules (LA)?
Methylphenidate hydrochloride extended-release capsules (LA) are a central nervous system (CNS) stimulant prescription medicine. It is used for the treatment of Attention Deficit Hyperactivity Disorder (ADHD).Methylphenidate hydrochloride extended-release capsules (LA) may help increase attention and decrease impulsiveness and hyperactivity in patients with ADHD.
Methylphenidate hydrochloride extended-release capsules (LA) should be used as a part of a total treatment program for ADHD that may include counseling or other therapies.
It is not known if methylphenidate hydrochloride extended-release capsules (LA) is safe and effective in children under 6 years of age.

Who should not take methylphenidate hydrochloride extended-release capsules (LA)?
Methylphenidate hydrochloride extended-release capsules (LA) should not be taken if you or your child:

- are allergic to methylphenidate hydrochloride, or any of the ingredients in methylphenidate hydrochloride extended-release capsules (LA). See the end of this Medication Guide for a complete list of ingredients in methylphenidate hydrochloride extended-release capsules (LA).
- are taking or have taken within the past 14 days an anti-depression medicine called a monoamine oxidase inhibitor (MAOI).

Methylphenidate hydrochloride extended-release capsules (LA) may not be right for you or your child. Before starting methylphenidate hydrochloride extended-release capsules (LA) tell your or your child's doctor about all health conditions (or a family history of), including:

- heart problems, heart defects, high blood pressure
- mental problems including psychosis, mania, bipolar illness, or depression
- circulation problems in fingers or toes
- if you are pregnant or plan to become pregnant. It is not known if methylphenidate hydrochloride extended-release capsules (LA) will harm your unborn baby.
  - There is a pregnancy registry for females who are exposed to ADHD medications, including methylphenidate hydrochloride extended-release capsules (LA) during pregnancy. The purpose of the registry is to collect information about the health of females exposed to methylphenidate hydrochloride extended-release capsules (LA) and their baby. If you or your child becomes pregnant during treatment with methylphenidate hydrochloride extended-release capsules (LA), talk to your healthcare provider about registering with the National Pregnancy Registry of ADHD medications at 1-866-961-2388 or visit online at https://womensmentalhealth.org/adhd-medications/.
- if you are breastfeeding or plan to breastfeed. Methylphenidate hydrochloride extended-release capsules (LA) passes into your breast milk. Talk to your healthcare provider about the best way to feed the baby during treatment with methylphenidate hydrochloride extended-release capsules (LA).

Tell your doctor about all of the medicines that you or your child take, including prescription and over-the-counter medicines, vitamins, and herbal supplements.Methylphenidate hydrochloride extended-release capsules (LA) and some medicines may interact with each other and cause serious side effects. Sometimes the doses of other medicines will need to be adjusted while taking methylphenidate hydrochloride extended-release capsules (LA).
Your doctor will decide whether methylphenidate hydrochloride extended-release capsules (LA) can be taken with other medicines.
Especially tell your doctor if you or your child takes:

- anti-depression medicines, including MAOIs
- blood pressure medicines (anti-hypertensive)
- risperidone

Know the medicines that you or your child takes. Keep a list of your medicines with you to show your doctor and pharmacist.

- You should not take methylphenidate hydrochloride extended-release capsules (LA) on the day of your operation if a certain type of anesthetic is used. This is because there is a chance of a sudden rise in blood pressure and heart rate during the operation.

Do not start any new medicine while taking methylphenidate hydrochloride extended-release capsules (LA) without talking to your doctor first.

How should methylphenidate hydrochloride extended-release capsules (LA) be taken?

- Take methylphenidate hydrochloride extended-release capsules (LA) exactly as prescribed. Your doctor may adjust the dose until it is right for you or your child.
- Take methylphenidate hydrochloride extended-release capsules (LA) once a day in the morning. Methylphenidate hydrochloride extended-release capsules (LA) is an extended-release capsule.
- Do not chew or crush methylphenidate hydrochloride extended-release capsules (LA) or the medicine inside the capsule.Swallow methylphenidate hydrochloride extended-release capsules (LA) whole with water or other liquids.
- If you cannot swallow the capsule whole, open it and sprinkle the medicine over a spoonful of applesauce. Swallow the applesauce and medicine mixture without chewing. Follow with a drink of water or other liquid.
- You should avoid drinking alcohol during treatment with methylphenidate hydrochloride extended-release capsules (LA) .This may cause a faster release of methylphenidate hydrochloride extended-release capsules (LA).
- From time-to-time, your doctor may stop methylphenidate hydrochloride extended-release capsules (LA) treatment for a while to check ADHD symptoms.
- Your doctor may do regular checks of the blood, heart, and blood pressure while taking methylphenidate hydrochloride extended-release capsules (LA). Children should have their height and weight checked often while taking methylphenidate hydrochloride extended-release capsules (LA). Methylphenidate hydrochloride extended-release capsules (LA) treatment may be stopped if a problem is found during these check-ups.

In case of poisoning, call your poison control center at 1-800-222-1222 right away or go to the nearest hospital emergency room.

What are possible side effects of methylphenidate hydrochloride extended-release capsules (LA)?

- see " What is the most important information I should know about methylphenidate hydrochloride extended-release capsules (LA)?" for information on reported heart and mental problems.
- painful and prolonged erections (priapism)have occurred with methylphenidate. If you or your child develops priapism, seek medical help right away. Because of the potential for lasting damage, priapism should be evaluated by a doctor immediately.
- circulation problems in fingers and toes(peripheral vasculopathy, including Raynaud's Phenomenon):
  - fingers or toes may feel numb, cool, painful
  - fingers or toes may change color from pale, to blue, to red

Tell your doctor if you or your child have numbness, pain, skin discoloration, or sensitivity to temperature in the fingers or toes.

- Call your doctor right away if you have or your child has any signs of unexplained wounds appearing on fingers or toes while taking methylphenidate hydrochloride extended-release capsules (LA).
- Slowing of growth (height and weight) in children

Common side effects include:

- fast heart beat
- sweating a lot

- Abnormal heartbeat (palpitations)
- Decreased appetite

- headache
- dry mouth

- trouble sleeping
- nausea

- nervousness
- stomach pain

Call your doctor for medical advice about side effects. You may report side effects to FDA at 1-800-FDA-1088.

How should I store methylphenidate hydrochloride extended-release capsules (LA)?

- Store methylphenidate hydrochloride extended-release capsules (LA) in a safe place and in a tightly closed container at room temperature, 68°F to 77°F (20°C to 25°C).
- Protect from moisture.
- Dispose of remaining, unused, or expired methylphenidate hydrochloride extended-release capsules (LA) by a medicine take-back program at authorized collection sites, such as retail pharmacies, hospital or clinic pharmacies, and law enforcement locations. If no take-back program or authorized collector is available, mix methylphenidate hydrochloride extended-release capsules (LA) with an undesirable, nontoxic substance, such as dirt, cat litter, or used coffee grounds to make it less appealing to children and pets. Place the mixture in a container, such as a sealed plastic bag and throw away (discard) methylphenidate hydrochloride extended-release capsules (LA) in the household trash.
- Keep methylphenidate hydrochloride extended-release capsules (LA) and all medicines out of the reach of children.

General information about the safe and effective use methylphenidate hydrochloride extended-release capsules (LA).
Medicines are sometimes prescribed for purposes other than those listed in a Medication Guide. You can ask your pharmacist or doctor for information about methylphenidate hydrochloride extended-release capsules (LA)that is written for healthcare professionals. Do not use methylphenidate extended release-capsules (LA) for a condition for which it was not prescribed. Do not give methylphenidate hydrochloride extended-release capsules (LA) to other people, even if they have the same symptoms. It may harm them and it is against the law.

What are the ingredients in methylphenidate hydrochloride extended-release capsules (LA)?
Active Ingredient: methylphenidate HCl
Inactive Ingredients:sugar spheres (which contain sucrose and starch (corn)), hypromellose, cellulose acetate butyrate, hypromellose acetate succinate, acetyltributyl citrate, acetone, talc, and purified water. Opaque gelatin capsules contain: titanium dioxide and gelatin. The 10mg capsule contains FD&C Green#3, FD&C #40, and FD&C Yellow #6. The 30 and 40 mg capsules contain D&C Red #28 and FD&C Blue #1. The capsules are imprinted with black ink which contains black iron oxide, shellac and potassium hydroxide. The 60 mg capsules contain iron oxide yellow and sodium lauryl sulfate. The capsules are imprinted with black ink which contains black iron oxide, shellac and potassium hydroxide. The 60 mg black imprinting ink also contains ammonium hydroxide and propylene glycol.
Distributed by:
Mayne Pharma
Raleigh, NC 27609
AB7678
For more information, call 1-844-825-8500.

This Medication Guide has been approved by the U.S. Food and Drug Administration.

Revised: 11/2022

PRINCIPAL DISPLAY PANEL - 60 mg Capsule Bottle Label

NDC 51862-614-30

Once Daily
Methylphenidate
Hydrochloride

CII

Extended-Release Capsules (LA)

60 mg

PHARMACIST: Please dispense with
Medication Guide provided separately.

Rx Only
30 Capsules

maynepharma

PRINCIPAL DISPLAY PANEL - 10 mg Capsule Bottle Label

NDC 51862-609-01

Once Daily
Methylphenidate
Hydrochloride

CII

Extended-Release Capsules (LA)

10 mg

PHARMACIST: Please dispense with
Medication Guide provided separately.

Rx Only
100 Capsules

maynepharma

PRINCIPAL DISPLAY PANEL - 20 mg Capsule Bottle Label

NDC 51862-610-01

Once Daily
Methylphenidate
Hydrochloride

CII

Extended-Release Capsules (LA)

20 mg

PHARMACIST: Please dispense with
Medication Guide provided separately.

Rx Only
100 Capsules

maynepharma

PRINCIPAL DISPLAY PANEL - 30 mg Capsule Bottle Label

NDC 51862-611-01

Once Daily
Methylphenidate
Hydrochloride

CII

Extended-Release Capsules (LA)

30 mg

PHARMACIST: Please dispense with
Medication Guide provided separately.

Rx Only
100 Capsules

maynepharma

PRINCIPAL DISPLAY PANEL - 40 mg Capsule Bottle Label

NDC 51862-612-01

Once Daily
Methylphenidate
Hydrochloride

CII

Extended-Release Capsules (LA)

40 mg

PHARMACIST: Please dispense with
Medication Guide provided separately.

Rx Only
100 Capsules

maynepharma